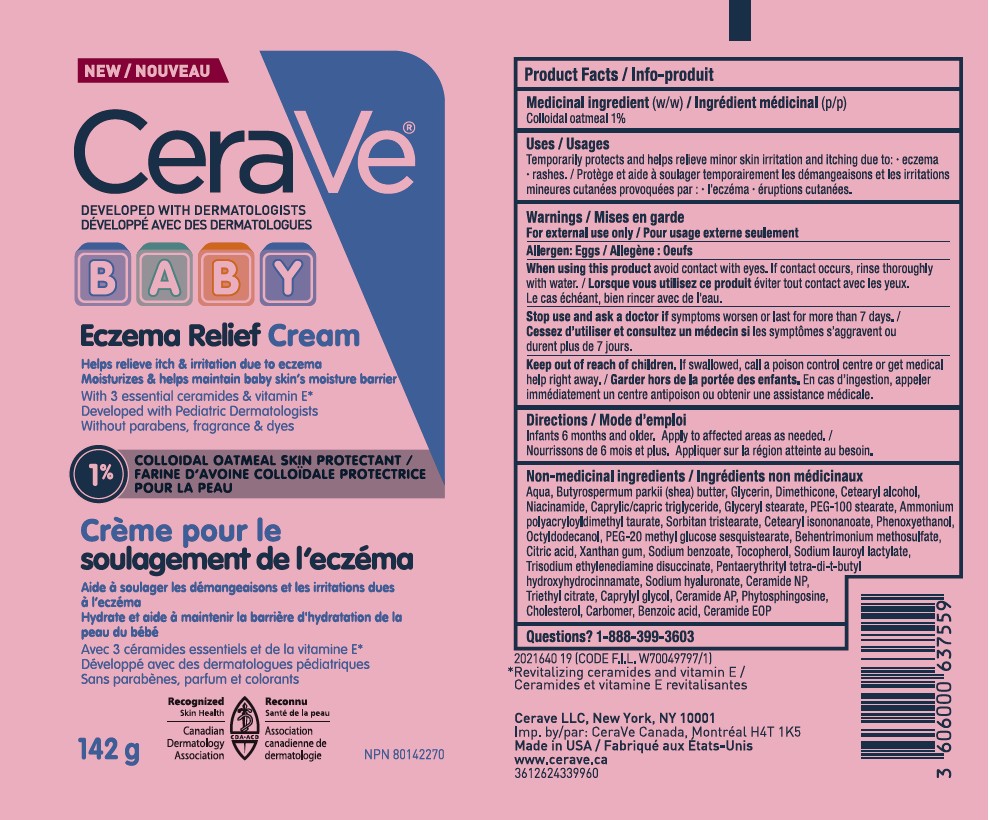 DRUG LABEL: CeraVe Developed With Dermatologist Baby Eczema Relief Cream
NDC: 82046-559 | Form: CREAM
Manufacturer: L'Oreal USA Products Inc
Category: otc | Type: HUMAN OTC DRUG LABEL
Date: 20251212

ACTIVE INGREDIENTS: OATMEAL 10 mg/1 g
INACTIVE INGREDIENTS: WATER; BUTYROSPERMUM PARKII (SHEA) BUTTER; GLYCERIN; DIMETHICONE; CETEARYL ALCOHOL; NIACINAMIDE; CAPRYLIC/CAPRIC TRIGLYCERIDE; GLYCERYL STEARATE; PEG-100 STEARATE; AMMONIUM POLYACRYLOYLDIMETHYL TAURATE; SORBITAN TRISTEARATE; CETEARYL ISONONANOATE; PHENOXYETHANOL; OCTYLDODECANOL; PEG-20 METHYL GLUCOSE SESQUISTEARATE; BEHENTRIMONIUM METHOSULFATE; CITRIC ACID; XANTHAN GUM; SODIUM BENZOATE; TOCOPHEROL; SODIUM LAUROYL LACTYLATE; TRISODIUM ETHYLENEDIAMINE DISUCCINATE; PENTAERYTHRITYL TETRA-DI-T-BUTYL HYDROXYHYDROCINNAMATE; SODIUM HYALURONATE; CERAMIDE NP; TRIETHYL CITRATE; CAPRYLYL GLYCOL; CERAMIDE AP; PHYTOSPHINGOSINE; CHOLESTEROL; CARBOMER; BENZOIC ACID

Drug Facts

Medicinal ingredient (w/w) / Ingrédient médicinal (p/p)

Colloidal oatmeal 1%

Uses / Usages

Temporarily protects and helps relieve minor skin irritation and itching due to: - eczema - rashes. / Protège et aide à soulager temporairement les démangeaisons et les irritations mineures cutanées provoquées par : - l'eczéma - éruptions cutanées.

Warnings / Mises en garde

For external use only/Pour usage externe seulement

Allergen: Eggs / Allergène : Oeufs

When using this product

avoid contact with eyes. If contact occurs, rinse thoroughly with water. / Lorsque vous utilisez ce produit éviter tout contact avec les yeux. Le cas échéant, bien rincer avec de l'eau.

Stop use and ask a doctor if

symptoms worsen or last for more than 7 days. / Cessez d'utiliser et consultez un médecin si les symptômes s'aggravent ou durent plus de 7 jours.

Keep out of reach of children.

If swallowed, call a poison control centre or get medical help right away. / Garder hors de la portée des enfants. En cas d'ingestion, appeler immédiatement un centre antipoison ou obtenir une assistance médicale.

Directions / Mode d'emploi

Infants 6 months and older. Apply to affected areas as needed. / Nourrissons de 6 mois et plus. Appliquer sur la région atteinte au besoin.

Non-medicinal ingredients / Ingrédients non médicinaux

Aqua, Butyrospermum parkii (shea) butter, Glycerin, Dimethicone, Cetearyl alcohol, Niacinamide, Caprylic/capric triglyceride, Glyceryl stearate, PEG-100 stearate, Ammonium polyacryloyldimethyl taurate, Sorbitan tristearate, Cetearyl isononanoate, Phenoxyethanol, Octyldodecanol, PEG-20 methyl glucose sesquistearate, Behentrimonium methosulfate, Citric acid, Xanthan gum, Sodium benzoate, Tocopherol, Sodium lauroyl lactylate, Trisodium ethylenediamine disuccinate, Pentaerythrityl tetra-di-t-butyl hydroxyhydrocinnamate, Sodium hyaluronate, Ceramide NP, Triethyl citrate, Caprylyl glycol, Ceramide AP, Phytosphingosine, Cholesterol, Carbomer, Benzoic acid, Ceramide EOP

Questions?

1-888-399-3603